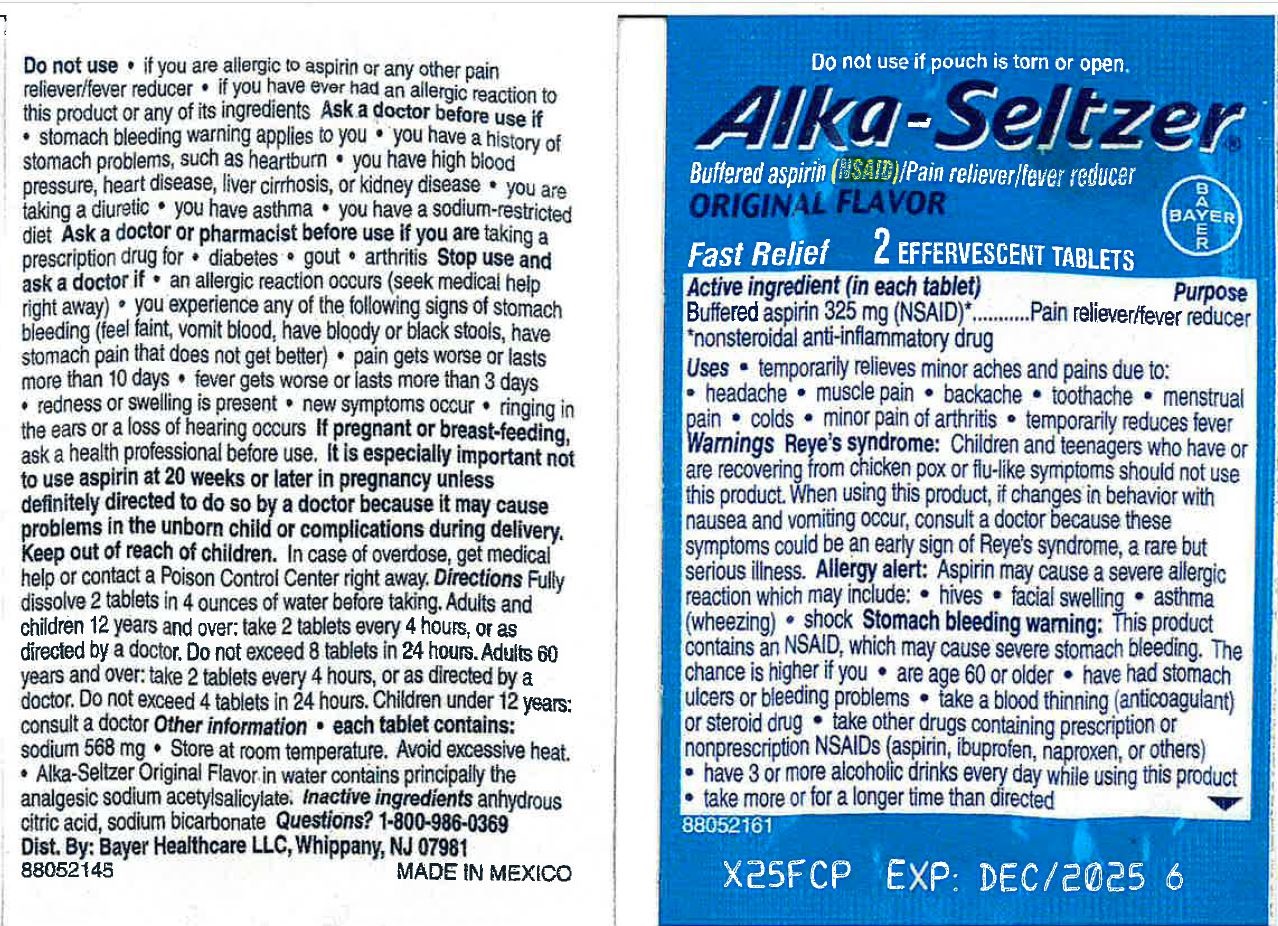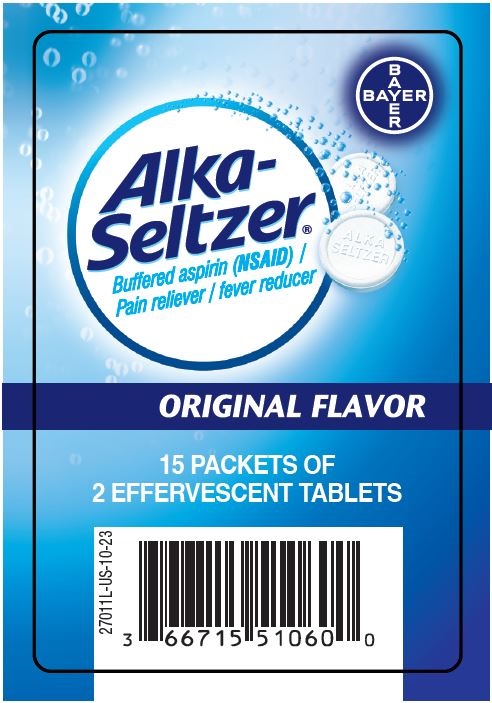 DRUG LABEL: Alka-Seltzer
NDC: 66715-5206 | Form: TABLET, EFFERVESCENT
Manufacturer: Lil' Drug Store Products, Inc.
Category: otc | Type: HUMAN OTC DRUG LABEL
Date: 20231214

ACTIVE INGREDIENTS: ASPIRIN 325 mg/1 1
INACTIVE INGREDIENTS: SODIUM BICARBONATE; ANHYDROUS CITRIC ACID

Alka-Seltzer®

Pouch Header/PDP

Do not use if pouch is torn or open.

Alka-Seltzer®

Buffered aspirin (NSAID)/Pain reliever/fever reducer

ORIGINAL FLAVOR

[Bayer logo]

Fast Relief

2 EFFERVESCENT TABLETS

Active ingredient

Active ingredient (in each tablet)

Buffered aspirin 325 mg (NSAID)*

*nonsteroidal anti-inflammatory drug

Purpose

Pain reliever/fever reducer

Uses

- temporarily relieves minor aches and pains due to:
- headache
- muscle pain
- backache
- toothache
- menstrual pain
- colds
- minor pain of arthritis
- temporarily reduces fever

Warnings

Reye's syndrome: Children and teenagers who have or are recovering from chicken pox or flu-like symptoms should not use this product. When using this product, if changes in behavior with nausea and vomiting occur, consult a doctor because these symptoms could be an early sign of Reye’s syndrome, a rare but serious illness.

Allergy alert

Allergy alert: Aspirin may cause a severe allergic reaction which may include:

- hives
- facial swelling
- asthma (wheezing)
- shock

Stomach bleeding warning: This product contains an NSAID, which may cause severe stomach bleeding. The chance is higher if you

- are age 60 or older
- have had stomach ulcers or bleeding problems
- take a blood thinning (anticoagulant) or steroid drug
- take other drugs containing prescription or nonprescription NSAIDs (aspirin, ibuprofen, naproxen, or others)
- have 3 or more alcoholic drinks every day while using this product
- take more or for a longer time than directedStomach bleeding warning: This product contains an NSAID, which

Do not use

- if you are allergic to aspirin or any other pain reliever/fever reducer
- if you have ever had an allergic reaction to this product or any of its ingredients

Ask a doctor before use if

- stomach bleeding warning applies to you
- you have a history of stomach problems, such as heartburn
- you have high blood pressure, heart disease, liver cirrhosis, or kidney disease
- you are taking a diuretic
- you have asthma
- you have a sodium-restricted diet

Ask a doctor or pharmacist before use if you are taking a prescription drug for

- diabetes
- gout
- arthritis

Stop use and ask a doctor if

- an allergic reaction occurs. Seek medical help right away.
- you experience any of the following signs of stomach bleeding:
- feel faint
- vomit blood
- have bloody or black stools
- have stomach pain that does not get better
- pain gets worse or lasts more than 10 days
- fever gets worse or lasts more than 3 days
- redness or swelling is present
- new symptoms occur
- ringing in the ears or a loss of hearing occurs

If pregnant or breast-feeding, ask a health professional before use.
It is especially important not to use aspirin at 20 weeks or later in pregnancy unless definitely directed to do so by a doctor
because it may cause problems in the unborn child or complications during delivery.

Keep out of reach of children. In case of overdose, get medical help or contact a Poison Control Center right away.

Directions

Directions Fully dissolve 2 tablets in 4 ounces of water before taking. Adults and children 12 years and over: take 2 tablets every 4 hours, or as directed by a doctor. Do not exceed 8 tablets in 24 hours. Adults 60 years and over: take 2 tablets every 4 hours, or as directed by a doctor. Do not exceed 4 tablets in 24 hours. Children under 12 years: consult a doctor.

Other information

- each tablet contains: sodium 568 mg
- store at room temperature. Avoid excessive heat.
- Alka-Seltzer Original Flavor in water contains principally the analgesic sodium acetylsalicylate

Inactive ingredients

Inactive ingredients anhydrous citric acid, sodium bicarbonate

Questions?

Questions? 1-800-986-0369 Dist. By Bayer Healthcare LLC, Whippany, NJ 07981

Alka-Seltzer® Gravity Sleeve (unit dose) - PDP/Label

[Bayer logo]

Alka-

Seltzer®

Buffered aspirin (NSAID)/

Pain reliever/fever reducer

ORIGINAL FLAVOR

15 PACKETS OF

2 EFFERVESCENT TABLETS

[UPC]